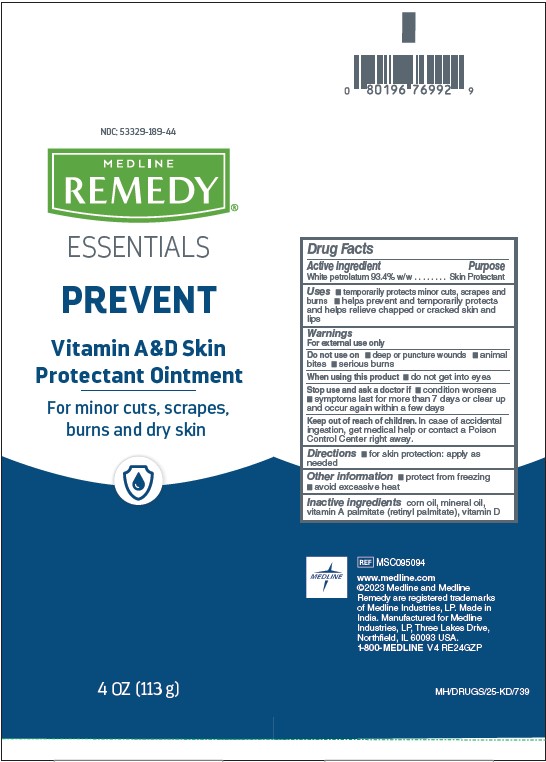 DRUG LABEL: Medline
NDC: 53329-189 | Form: OINTMENT
Manufacturer: Medline Industries, LP
Category: otc | Type: HUMAN OTC DRUG LABEL
Date: 20241010

ACTIVE INGREDIENTS: PETROLATUM 93.4 g/100 g
INACTIVE INGREDIENTS: VITAMIN D; MINERAL OIL; VITAMIN A PALMITATE; CORN OIL

189 Vitamin A&D Skin Protectant Ointment

Active ingredient

White petrolatum 93.4% w/w

Purpose

Skin Protectant

Uses

- temporarily protects minor cuts, scrapes and burns
- helps prevent and temporarily protects and helps relieve chapped or cracked skin and lips

Warnings

For external use only

Do not use on

- deep or puncture wounds
- animal bites
- serious burns

When using this product

- do not get into eyes

Stop use and ask a doctor if

- condition worsens
- symptoms last for more than 7 days or clear up and occur again within a few days

Keep out of reach of children.

In case of accidental ingestion, get medical help or contact a Poison Control Center right away.

Directions

for skin protectant: apply as needed

Other information

- protect from freezing
- avoid excessive heat

Inactive ingredients

corn oil, mineral oil, vitamin A palmitate (retinyl palmitate), vitamin D